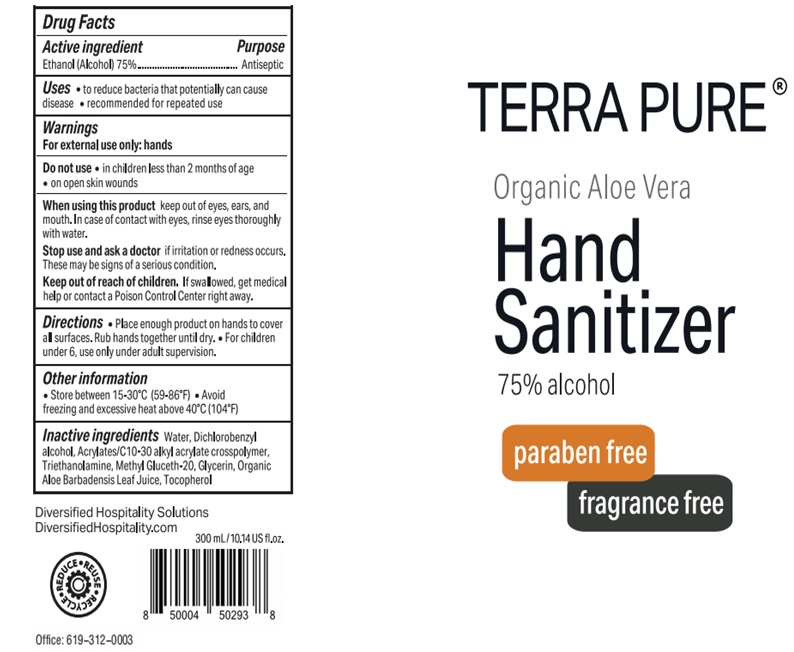 DRUG LABEL: Terra Pure Organic Aloe Vera Hand Sanitizer 75 Alcohol
NDC: 77849-003 | Form: GEL
Manufacturer: Yangzhou ECO-Amenities CO., Ltd
Category: otc | Type: HUMAN OTC DRUG LABEL
Date: 20200714

ACTIVE INGREDIENTS: ALCOHOL 0.75 mL/1 mL
INACTIVE INGREDIENTS: WATER; DICHLOROBENZYL ALCOHOL; CARBOMER INTERPOLYMER TYPE A (ALLYL SUCROSE CROSSLINKED); TROLAMINE; METHYL GLUCETH-20; GLYCERIN; ALOE VERA LEAF; TOCOPHEROL

Terra Pure Organic Aloe Vera Hand Sanitizer, 75% Alcohol

Active ingredient

Ethanol (Alcohol) 75%

Purpose

Antiseptic

Use

- to reduce bacteria that potentially can cause disease
- recommended for repeated use

Warnings

For external use only: hands

Do not use

- in children less than 2 months of age.
- on open skin wounds

When using this product

keep out of eyes, ears, and mouth. In case of contact with eyes, rinse eyes thoroughly with water.

Stop use and ask a doctor

if irritation or redness occurs. These may be signs of a serious condition.

Keep out of reach of children.

If swallowed, get medical help or contact a Poison Control Center right away.

Directions

- Place enough product on hands to cover all surfaces. Rub hands together until dry.
- For children under 6, use only under adult supervision.

Other information

- Store between 15-30°C (59-86°F)
- Avoid freezing and excessive heat above 40°C (104°F)

Inactive ingredients

Water, Dichlorobenzyl alcohol, Acrylates/C10-30 Alkyl acrylate crosspolymer, Triethanomaine, Methyl Gluceth-20, Glycerin, Organic Aloe Barbadensis Leaf Juice, Tocopherol